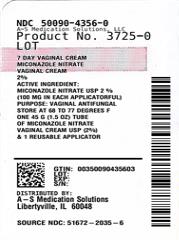 DRUG LABEL: Miconazole Nitrate
NDC: 50090-4356 | Form: CREAM
Manufacturer: A-S Medication Solutions
Category: otc | Type: HUMAN OTC DRUG LABEL
Date: 20260219

ACTIVE INGREDIENTS: MICONAZOLE NITRATE 20 mg/1 g
INACTIVE INGREDIENTS: BHT; MINERAL OIL; WATER; BENZOIC ACID

Miconazole Nitrate

Drug Facts

Active ingredient

Miconazole nitrate USP 2% (100 mg in each applicatorful)

Purpose

Vaginal antifungal

Uses

- treats vaginal yeast infections
- relieves external itching and irritation due to a vaginal yeast infection

Warnings

For vaginal use only

Do not use if you have never had a vaginal yeast infection diagnosed by a doctor

Ask a doctor before use if you have

- vaginal itching and discomfort for the first time
- lower abdominal, back or shoulder pain, fever, chills, nausea, vomiting, or foul-smelling vaginal discharge. You may have a more serious condition.
- vaginal yeast infections often (such as once a month or 3 in 6 months). You could be pregnant or have a serious underlying medical cause for your symptoms, including diabetes or a weakened immune system.
- been exposed to the human immunodeficiency virus (HIV) that causes AIDS

Ask a doctor or pharmacist before use if you aretaking the prescription blood thinning medicine warfarin, because bleeding or bruising may occur

When using this product

- do not use tampons, douches, spermicides, or other vaginal products. Condoms and diaphragms may be damaged and fail to prevent pregnancy or sexually transmitted diseases (STDs).
- do not have vaginal intercourse
- mild increase in vaginal burning, itching or irritation may occur
- if you do not get complete relief ask a doctor before using another product

Stop use and ask a doctor if

- symptoms do not get better in 3 days
- symptoms last more than 7 days
- you get a rash or hives, abdominal pain, fever, chills, nausea, vomiting, or foul-smelling vaginal discharge.

PREGNANCY OR BREAST FEEDING

If pregnant or breast-feeding,ask a health professional before use.

Keep out of reach of children.If swallowed, get medical help or contact a Poison Control Center (1-800-222-1222) right away.

Directions

- before using this product read the enclosed consumer information leaflet for complete directions and information
- adults and children 12 years of age and over:
  - applicator:insert 1 applicatorful into the vagina at bedtime for 7 nights in a row. Wash applicator after use.
  - use the same tube of cream if you have itching and irritation on the skin outside the vagina. Squeeze a small amount of cream onto your fingertip. Apply to itchy, irritated skin outside the vagina (vulva). Use 2 times daily for up to 7 days as needed.
- children under 12 years of age: ask a doctor

Other information

- do not purchase if carton is opened
- do not use if seal over tube opening has been punctured or is not visible
- store at 20° to 25°C (68° to 77°F)
- see carton or tube crimp for lot number and expiration date

Inactive ingredients

benzoic acid (0.20%) as a preservative, butylated hydroxytoluene, mineral oil, oleoyl polyoxylglyceride, PEG-6-32 stearate/glycol stearate, and purified water.

Questions?

call 1-866-923-4914

Distributed by:
Taro Pharmaceuticals U.S.A., Inc.
Hawthorne, NY 10532

HOW SUPPLIED

Product: 50090-4356

NDC: 50090-4356-0 45 g in a TUBE, WITH APPLICATOR / 1 in a CARTON